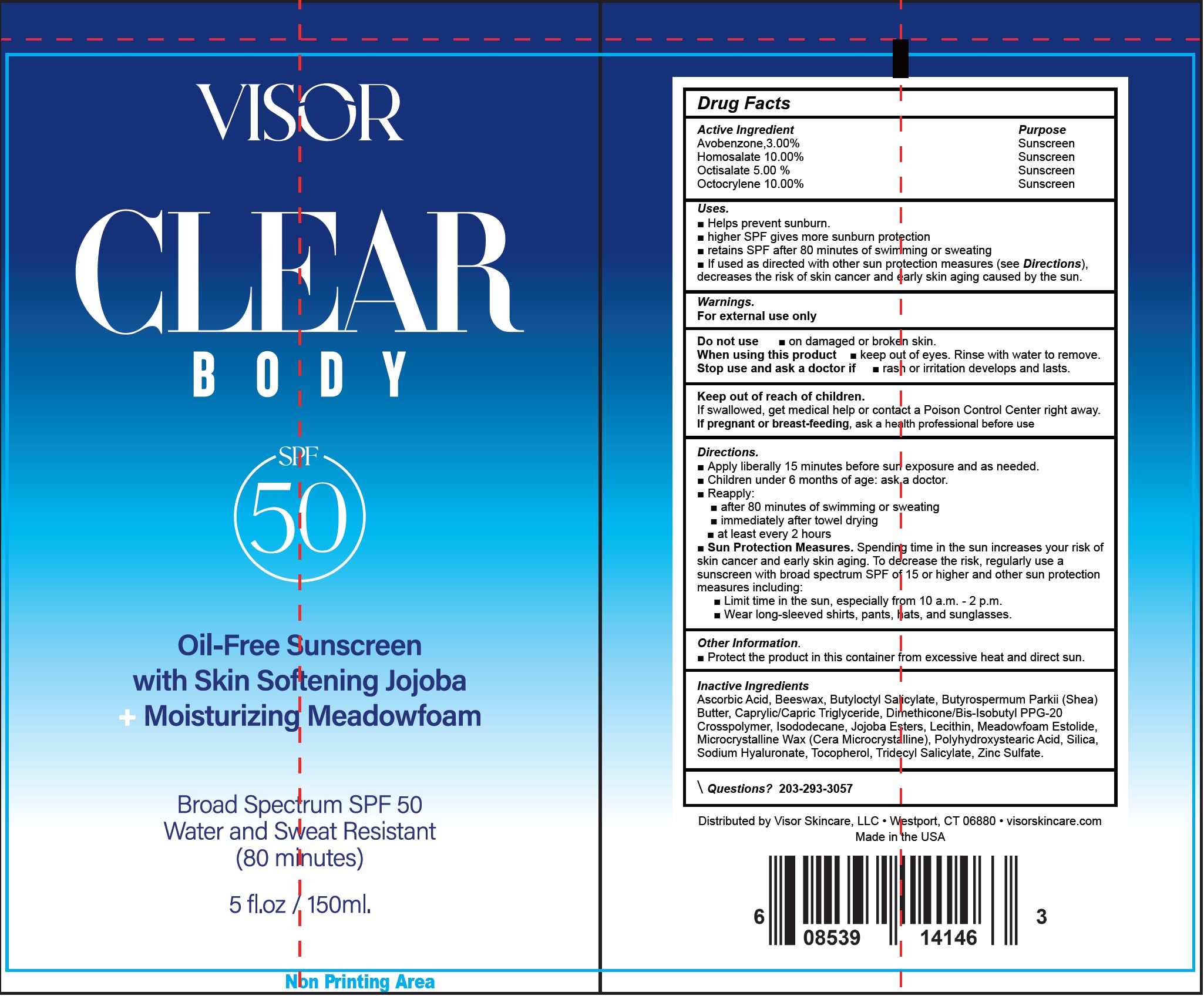 DRUG LABEL: Visor Clear Body Oil-Free Sunscreen SPF 50
NDC: 85335-589 | Form: GEL
Manufacturer: VISOR SKINCARE LLC
Category: otc | Type: HUMAN OTC DRUG LABEL
Date: 20250312

ACTIVE INGREDIENTS: AVOBENZONE 30 mg/1 mL; HOMOSALATE 100 mg/1 mL; OCTISALATE 50 mg/1 mL; OCTOCRYLENE 100 mg/1 mL
INACTIVE INGREDIENTS: ASCORBIC ACID; YELLOW WAX; BUTYLOCTYL SALICYLATE; SHEA BUTTER; MEDIUM-CHAIN TRIGLYCERIDES; ISODODECANE; MEADOWFOAM ESTOLIDE; MICROCRYSTALLINE WAX; SILICON DIOXIDE; HYALURONATE SODIUM; TOCOPHEROL; TRIDECYL SALICYLATE; ZINC SULFATE

Visor Clear Body Oil-Free Sunscreen SPF 50

Active ingredient

Avobenzone, 3.00%
Homosalate 10.00%
Octisalate 5.00%
Octocrylene 10.00%

Purpose

Sunscreen

Uses.

- Helps prevent sunburn.
- higher SPF gives more sunburn protection
- retains SPF after 80 minutes of swimming or sweating
- If used as directed with other sun protection measures (see Directions), decreases the risk of skin cancer and early skin agingcaused by the sun.

Warnings

For external use only

Do not use

- on damaged or broken skin.

When using this product

- keep out of eyes. Rinse with water to remove.

Stop use and ask a doctor if

- rash or irritation develops and lasts.

Keep out of reach of children.

If swallowed, get medical help or contact a Poison Control Center right away.

If pregnant or breast-feeding,

ask a health professional before use

Directions

- Apply liberally 15 minutes before sun exposure and as needed.
- Children under 6 months of age: ask a doctor.
- Reapply:
- after 80 minutes of swimming or sweating
- immediately after towel drying
- at least every 2 hours
- Sun Protection Measures.Spending time in the sun increase your risk of skin cancer and early skin aging. To decrease this risk, regularly use a sunscreen with a broad spectrum SPF of 15 or higher and other sun protection measures including:
- Limit time in the sun, especially from 10 a.m.-2p.m.
- Wear long-sleeved shirts, pants,hats,and sunglasses.

Other information

- Protect the product in this container from excessive heat and direct sun.

Inactive Ingredients

Ascorbic Acid, Beeswax, Butyloctyl Salicylate, Butyrospermum Parkii (Shea) Butter, Caprylic/Capric Triglyceride, Dimethicone/Bis-Isobutyl PPG-20 Crosspolymer, Isododecane, Jojoba Esters, Lecithin, Meadowfoam Estolide, Microcrystalline Wax (Cera Microcrystalline), Polyhydroxystearic Acid, Silica, Sodium Hyaluronate, Tocopherol, Tridecyl Salicylate, Zinc Sulfate.

Questions?

Call 203-293-3057